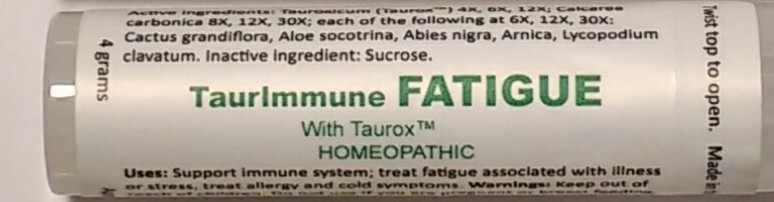 DRUG LABEL: TaurImmune Fatigue
NDC: 73311-140 | Form: PELLET
Manufacturer: CureImmune
Category: homeopathic | Type: HUMAN OTC DRUG LABEL
Date: 20250127

ACTIVE INGREDIENTS: ARNICA MONTANA 6 [hp_X]/1 1; ALOE 6 [hp_X]/1 1; PICEA MARIANA RESIN 6 [hp_X]/1 1; LYCOPODIUM CLAVATUM SPORE 6 [hp_X]/1 1; SELENICEREUS GRANDIFLORUS STEM 6 [hp_X]/1 1; OYSTER SHELL CALCIUM CARBONATE, CRUDE 8 [hp_X]/1 1; ZINC CARBOBENZOXY-.BETA.-ALANYLTAURINATE 4 [hp_X]/1 1
INACTIVE INGREDIENTS: SUCROSE

Taurimmune fatigue pellet

Active Ingredients

Abies nig 6X, 12X, 30X

Aloe 6X, 12X, 30X

Arnica 6X, 12X, 30X

Cactus 6X, 12X, 30X
Lycopodium 6X, 12X, 30X

Tauroxicum 4X, 12X, 30X

Calc. carb. 8X 12X, 30X.

Use

Support immune system; treat fatigue associated with illness or stress; treat allergy and cold symptoms.

PURPOSE

For treatment of moderate to severe fatigue due to illness or other conditions. Immune support. May also help treat symptoms of colds, flu and allergies.

Directions

Directions for adults and children 15 years of age and older: Hold upside down and twist cap to release pellets into cap. Take 2 pellets once daily or as directed. Best if taken early in the day. Take apart from food and drinks. See package insert for details.

Warnings

Keep out of reach of children. Do not use if you are pregnant or breast feeding, an organ recipient, using immune-suppressive drugs, or if the cap seal is not intact. See package insert for details.

Keep out of reach of children.

Inactive Ingredients

Sucrose

Disclaimer

Claims based on traditional
homeopathic practice, not accepted
medical evidence. Not FDA evaluated.

PACKAGE LABEL

TaurImmune

FATIGUE

With Taurox
HOMEOPATHIC

4 grams